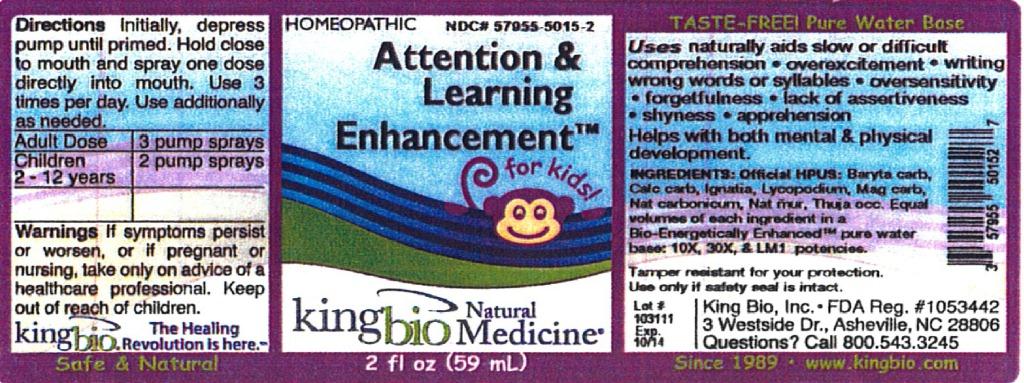 DRUG LABEL: Attention and Learning Enhancement
NDC: 57955-5015 | Form: LIQUID
Manufacturer: King Bio Inc.
Category: homeopathic | Type: HUMAN OTC DRUG LABEL
Date: 20120402

ACTIVE INGREDIENTS: BARIUM CARBONATE 10 [hp_X]/59 mL; OYSTER SHELL CALCIUM CARBONATE, CRUDE 10 [hp_X]/59 mL; STRYCHNOS IGNATII SEED 10 [hp_X]/59 mL; LYCOPODIUM CLAVATUM SPORE 10 [hp_X]/59 mL; MAGNESIUM CARBONATE 10 [hp_X]/59 mL; SODIUM CARBONATE 10 [hp_X]/59 mL; SODIUM CHLORIDE 10 [hp_X]/59 mL; THUJA OCCIDENTALIS LEAFY TWIG 10 [hp_X]/59 mL
INACTIVE INGREDIENTS: WATER

Attention and Learning Enhancement

Active Ingredients

Official HPUS: Baryta carbonica, Calcarea carbonica, Ignatia amara, Lycopodium clavatum, Magnesia carbonica, Natrum carbonicum, Natrum muriaticum and Thuja occidentalis.

Reference image attention.jpg

Inactive Ingredient

Equal volumes of each ingredient in a Bio-Energetically Enhanced pure water base: 10X, 30X, and LM1 potencies.
Reference image attention.jpg

Purpose

Uses naturally aids:

- slow or difficult comprehension
- overexcitement
- writing wrong words or syllables
- oversensitivity
- forgetfulness
- lack of assertiveness
- shyness
- apprehension

Helps with both mental and physical development.
Reference image attention.jpg

Directions

Initially, depress pump until primed. Hold close to mouth and spray one dose directly into mouth. Use 3 times per day. Use additionally as needed.

Adult Dose 3 pump sprays

Children 2-12 years 2 pump sprays

Reference image attention.jpg

Warnings

If symptoms persist or worsen, or if pregnant or nursing, take only on advice of a healthcare professional.

Other: Tamper resistant for your protection. Use only if safety seal is intact.

Reference image attention.jpg

Keep out of reach of children.

Reference image attention.jpg

Indications and Usage

Uses naturally aids slow or difficult comprehension, overexcitement, writing wrong words or syllables, oversensitivity, forgetfulness, lack of assertiveness, shyness, and apprehension.

Helps with both mental and physical development.

Reference image attention.jpg

PACKAGE LABEL

King Bio Inc.

3 Westside Drive

Asheville, NC 28806

Questions? Call 800.543.3245

www.kingbio.com